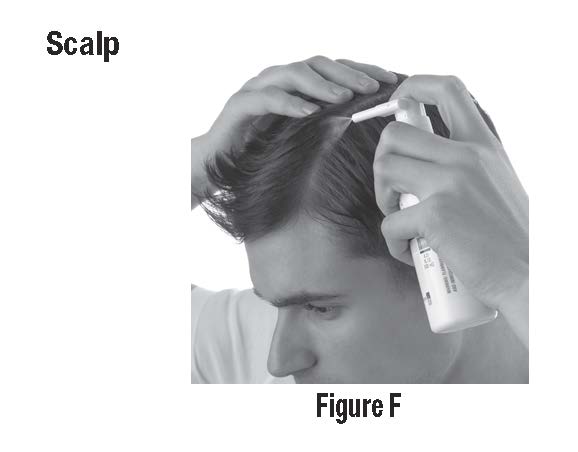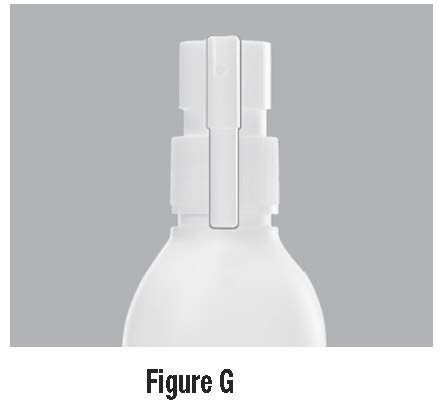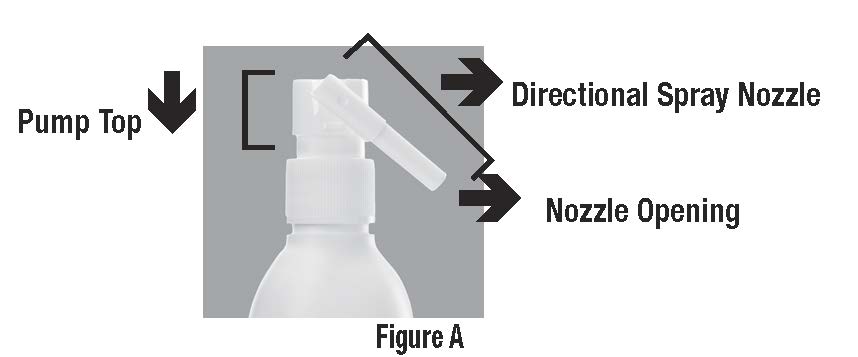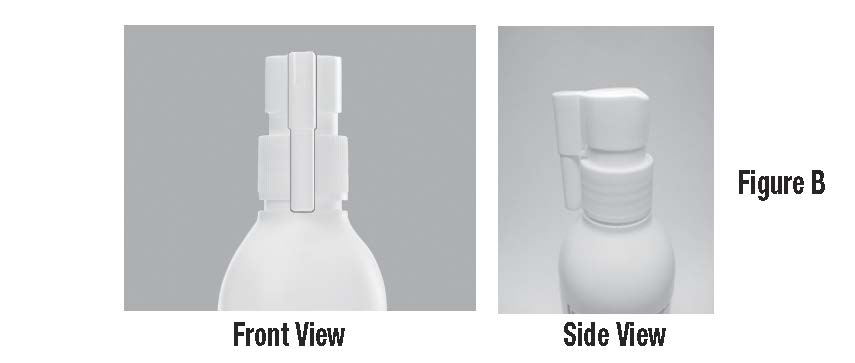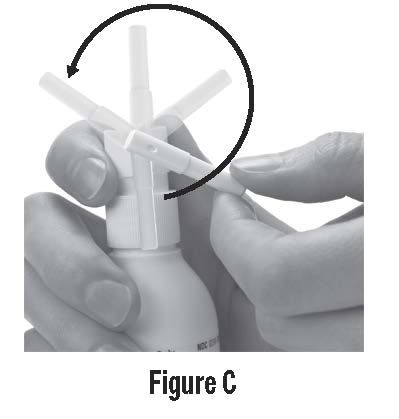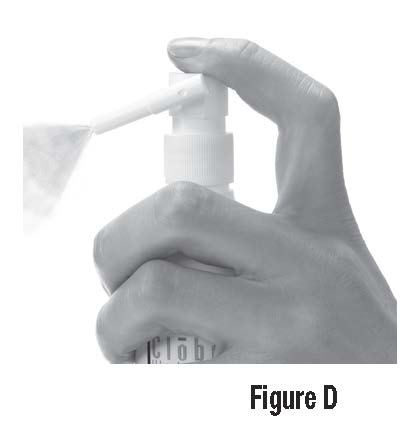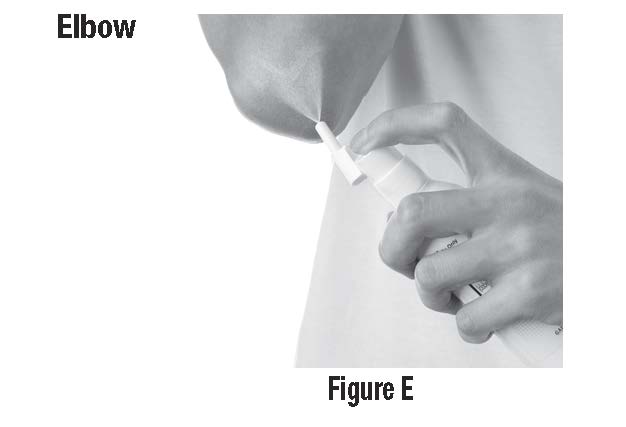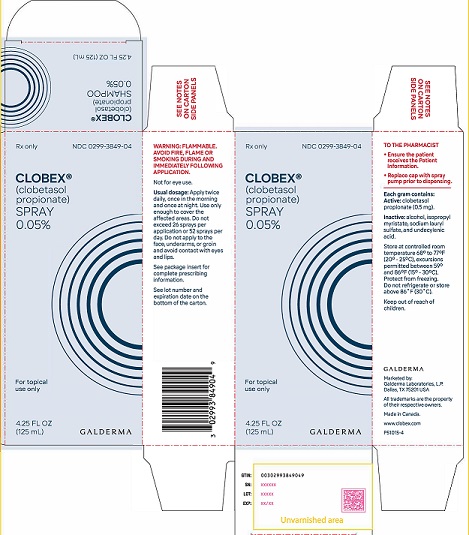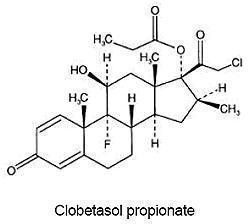 DRUG LABEL: CLOBEX
NDC: 0299-3849 | Form: SPRAY
Manufacturer: Galderma Laboratories, L.P.
Category: prescription | Type: HUMAN PRESCRIPTION DRUG LABEL
Date: 20241024

ACTIVE INGREDIENTS: CLOBETASOL PROPIONATE 0.05 g/1 mL
INACTIVE INGREDIENTS: ALCOHOL; ISOPROPYL MYRISTATE; SODIUM LAURYL SULFATE; UNDECYLENIC ACID

HIGHLIGHTS OF PRESCRIBING INFORMATION

These highlights do not include all the information needed to use CLOBEX®(clobetasol propionate) Spray, 0.05% safely and effectively. See full prescribing information for CLOBEX®(clobetasol propionate) Spray, 0.05%. CLOBEX spray, for topical use. Initial U.S. Approval: 1985

1 INDICATIONS AND USAGE

CLOBEX®(clobetasol propionate) Spray, 0.05% is a corticosteroid indicated for the topical treatment of moderate to severe plaque psoriasis affecting up to 20% body surface area (BSA) in patients 18 years of age or older (1.1)
Limitations of Use:

- Do not use on the face, axillae or groin. (1.2)
- Do not use if atrophy is present at the treatment site. (1.2)
- Do not use for rosacea or perioral dermatitis. (1.2)

2 DOSAGE AND ADMINISTRATION

- Not for oral, ophthalmic, or intravaginal use. (1.2)
- Sprayed directly onto the affected skin areas twice daily and rub in gently. (2)
- The total dosage should not exceed 50 g (59 mL or 2 fluid ounces) per week. Do not use more than 26 sprays per application or 52 sprays per day. (2)
- Treatment beyond 2 weeks should be limited to localized lesions of moderate to severe plaque psoriasis that have not sufficiently improved after the initial 2 weeks of treatment with CLOBEX®Spray, 0.05%. (2)
- Do not use for more than 4 weeks. (2)

3 DOSAGE FORMS AND STRENGTHS

Spray, 0.05% w/w (3)

4 CONTRAINDICATIONS

None.

5 WARNINGS AND PRECAUTIONS

- Clobetasol propionate is a highly potent topical corticosteroid that has been shown to suppress the HPA axis at the lowest doses tested. (5.1)
- Cushing’s syndrome, hyperglycemia, and unmasking of latent diabetes mellitus can also result from systemic absorption of topical corticosteroids. (5.1)
- Systemic absorption may require periodic evaluation for HPA axis suppression. Modify use if HPA axis suppression develops. (5.1)
- Children may be more susceptible to systemic toxicity from use of topical corticosteroids. (5.1,8.4)
- CLOBEX Spray may increase the risk of cataract and glaucoma. If visual symptoms occur, consider referral to an ophthalmologist. (5.2)
- Local adverse reactions with topical corticosteroids may occur more frequently with the use of occlusive dressings and higher potency corticosteroids, including clobetasol propionate (5.3)
- CLOBEX®Spray is flammable, keep away from heat or flame. (5.6)

6 ADVERSE REACTIONS

In controlled, clinical trials with CLOBEX®Spray, 0.05%, the most common adverse reactions (incidence > 2%) were burning, pruritus, nasopharyngitis, upper respiratory tract infection. (6.1)

To report SUSPECTED ADVERSE REACTIONS, contact Galderma Laboratories, L.P. at 1-866-735-4137 or FDA at 1-800-FDA-1088 or www.fda.gov/medwatch.

FULL PRESCRIBING INFORMATION

1 INDICATIONS AND USAGE

1.1 Indication

CLOBEX®Spray, 0.05% is a super-high potent topical corticosteroid formulation indicated for the treatment of moderate to severe plaque psoriasis affecting up to 20% body surface area (BSA) in patients 18 years of age or older.

Patients should be instructed to use CLOBEX®Spray, 0.05% for the minimum amount of time necessary to achieve the desired results see [ Dosage and Administration (2)] .

Use in patients under 18 years of age is not recommended because safety has not been established and because numerically high rates of HPA axis suppression were seen with other clobetasol propionate topical formulations. [ see Use in Specific Populations (8.4)].

1.2 Limitations of Use

CLOBEX®Spray, 0.05% should not be used on the face, axillae, or groin. CLOBEX®Spray, 0.05% should not be used if there is atrophy at the treatment site. CLOBEX®Spray, 0.05% should not be used in the treatment of rosacea or perioral dermatitis.

2 DOSAGE AND ADMINISTRATION

CLOBEX®Spray, 0.05% is for topical use only, and not for ophthalmic, oral or intravaginal use.

CLOBEX®Spray, 0.05% should be sprayed directly onto the affected skin areas twice daily and rubbed in gently and completely.

The total dosage should not exceed 50 g (59 mL or 2 fluid ounces) per week because of the potential for the drug to suppress the hypothalamic-pituitary-adrenal (HPA) axis. Do not use more than 26 sprays per application or 52 sprays per day.

CLOBEX®Spray, 0.05% contains a topical corticosteroid; therefore treatment should be limited to 4 weeks. Therapy should be discontinued when control has been achieved. Treatment beyond 2 weeks should be limited to localized lesions of moderate to severe plaque psoriasis that have not sufficiently improved after the initial 2 weeks of treatment with CLOBEX®Spray, 0.05%. If no improvement is seen within 2 weeks, reassessment of diagnosis may be necessary. Before prescribing for more than 2 weeks, any additional benefits of extending treatment to 4 weeks should be weighed against the risk of HPA axis suppression.

Unless directed by physician, CLOBEX®Spray, 0.05% should not be used with occlusive dressings.

3 DOSAGE FORMS AND STRENGTHS

Spray, 0.05% w/w. Each gram of CLOBEX®Spray, 0.05% contains 0.5 mg of clobetasol propionate in a clear, colorless liquid.

4 CONTRAINDICATIONS

None.

5 WARNINGS AND PRECAUTIONS

5.1 Effects on the Endocrine System

Clobetasol propionate is a highly potent topical corticosteroid that has been shown to suppress the HPA axis at the lowest doses tested.

Systemic absorption of topical corticosteroids can produce reversible hypothalamic-pituitary-adrenal (HPA) axis suppression with the potential for clinical glucocorticosteroid insufficiency. This may occur during treatment or upon withdrawal of the topical corticosteroid.

In studies evaluating the potential for hypothalamic-pituitary-adrenal (HPA) axis suppression, using the Cosyntropin Stimulation Test, CLOBEX®Spray, 0.05% demonstrated rates of suppression that were comparable after 2 and 4 weeks of twice-daily use (19% and 15-20%, respectively), in adult patients with moderate to severe plaque psoriasis (≥ 20% BSA). In these studies, HPA axis suppression was defined as serum cortisol level ≤18 μg/dL 30-min post cosyntropin stimulation [see Clinical Pharmacology (12)] .

Because of the potential for systemic absorption, use of topical corticosteroids may require that patients be periodically evaluated for HPA axis suppression. Factors that predispose a patient using a topical corticosteroid to HPA axis suppression include the use of more potent steroids, use over large surface areas, use over prolonged periods, use under occlusion, use on an altered skin barrier, and use in patients with liver failure.

An ACTH stimulation test may be helpful in evaluating patients for HPA axis suppression. If HPA axis suppression is documented, an attempt should be made to gradually withdraw the drug, to reduce the frequency of application, or to substitute a less potent steroid. Manifestations of adrenal insufficiency may require supplemental systemic corticosteroids. Recovery of HPA axis function is generally prompt and complete upon discontinuation of topical corticosteroids.

Cushing’s syndrome, hyperglycemia, and unmasking of latent diabetes mellitus can also result from systemic absorption of topical corticosteroids.

Use of more than one corticosteroid-containing product at the same time may increase the total systemic corticosteroid exposure.

Pediatric patients may be more susceptible to systemic toxicity from use of topical corticosteroids [see Use in Specific Populations (8.4)] .

5.2 Ophthalmic Adverse Reactions

Use of topical corticosteroids, including CLOBEX Spray, may increase the risks of glaucoma and posterior subcapsular cataract. Glaucoma and cataracts have been reported in postmarketing experience with the use of topical corticosteroid products, including topical clobetasol products [see Adverse Reactions (6.2)].
Avoid contact of CLOBEX Spray with eyes. Advise patients to report any visual symptoms and consider referral to an ophthalmologist for evaluation.

5.3 Local Adverse Reactions with Topical Corticosteroids.

The following additional local adverse reactions have been reported with topical corticosteroids. They may occur more frequently with the use of occlusive dressings and higher potency corticosteroids, including clobetasol propionate. These reactions are listed in an approximate decreasing order of occurrence: folliculitis, acneiform eruptions, hypopigmentation, perioral dermatitis, allergic contact dermatitis, secondary infection, striae and miliaria.

5.4 Allergic Contact Dermatitis

Allergic contact dermatitis to any component of topical corticosteroids is usually diagnosed by a failure to heal rather than a clinical exacerbation. Clinical diagnosis of allergic contact dermatitis can be confirmed by patch testing.

5.5 Concomitant Skin Infections

In the presence of dermatological infections, the use of an appropriate antifungal or antibacterial agent should be instituted. If a favorable response does not occur promptly, use of CLOBEX®Spray, 0.05% should be discontinued until the infection has been adequately controlled.

5.6 Flammable Contents

CLOBEX®Spray, 0.05% is flammable; keep away from heat or flame.

6 ADVERSE REACTIONS

6.1 Clinical Trials Experience

Because clinical trials are conducted under widely varying conditions, adverse reaction rates observed in the clinical trials of a drug cannot be directly compared to rates in the clinical trials of another drug and may not reflect the rates observed in practice.

In controlled, clinical trials with CLOBEX®Spray, 0.05%, the most common adverse reaction was burning at the site of application [40% of subjects treated with CLOBEX®Spray, 0.05% and 47% of subjects treated with Spray Vehicle]. Other commonly reported adverse reactions for CLOBEX®Spray, 0.05% and Spray Vehicle, respectively, are noted in Table 1.

Table 1 - Commonly Occurring Adverse Reactions (≥1% Incidence)
 | Clobetasol Propionate | Vehicle Spray
Adverse Reaction | 0.05% Spray | (N=120)
 | (N=120)
System Organ Class
General disorders and administration site conditions | 50 (42%) | 56 (47%)
Application site burning | 48 (40%) | 56 (47%)
Application site dryness | 2 (2%) | 0 (0%)
Application site irritation | 1 (1%) | 0 (0%)
Application site pain | 1 (1%) | 2 (2%)
Application site pigmentation changes | 1 (1%) | 0 (0%)
Application site pruritus | 4 (3%) | 3 (3%)
Infections and infestations | 17 (14%) | 12 (10%)
Nasopharyngitis | 6 (5%) | 3 (3%)
Pharyngitis streptococcal | 1 (1%) | 0 (0%)
Upper respiratory tract infection | 10 (8%) | 2 (2%)
Skin and subcutaneous tissue disorders | 4 (3%) | 2 (2%)
Eczema asteatotic | 2 (2%) | 0 (0%)

Most local adverse reactions were rated as mild to moderate and they are not affected by age, race or gender.

Systemic absorption of topical corticosteroids has produced hypothalamic-pituitary-adrenal (HPA) axis suppression, manifestations of Cushing’s syndrome, hyperglycemia, and glucosuria in some patients.

6.2 Postmarketing Experience

Because these reactions are reported voluntarily from a population of uncertain size, it is not always possible to reliably estimate their frequency or establish a causal relationship to drug exposure.

The following adverse reactions have been identified during post-approval use of CLOBEX®Spray, 0.05%.

Skin:Burning, pruritus, erythema, pain, irritation, rash, peeling, urticaria, and contact dermatitis.

Ophthalmic adverse reactions of blurred vision, cataracts, glaucoma, increased intraocular pressure, and central serous chorioretinopathy have been reported with the use of topical corticosteroids.

8 USE IN SPECIFIC POPULATIONS

8.1 Pregnancy

Risk Summary

TERATOGENIC EFFECTS

There are no available data on CLOBEX® Spray use in pregnant women to identify a drug-associated risk of major birth defects, miscarriage, or adverse maternal or fetal outcomes.

Observational studies suggest an increased risk of low birthweight in infants with the maternal use of potent or very potent topical corticosteroids (see Data). Advise pregnant women that CLOBEX® Spray may increase the risk of having a low birth weight infant and to use CLOBEX® Spray on the smallest area of skin and for the shortest duration possible.
Animal reproduction studies have not been conducted with CLOBEX® Spray. In an animal reproduction study, subcutaneous administration of clobetasol propionate to pregnant rats at doses greater than 12.5 μg/kg/day during the period of organogenesis caused an increase in malformations (increased incidence of umbilical hernia) [see Data]. The available data do not allow calculation of relevant comparisons between the systemic exposure of clobetasol propionate in animal studies to the systemic exposure that would be expected in humans after topical use of CLOBEX® Spray.
The estimated background risk of major birth defects and miscarriage for the indicated population is unknown. All pregnancies have a background risk of birth defect, loss, or other adverse outcomes. In the U.S. general population, the estimated risk of major birth defects and miscarriage in clinically recognized pregnancies is 2 to 4% and 15 to 20%, respectively.

Data
Human Data
Available observational studies in pregnant women did not identify a drug-associated risk of major birth defects, preterm delivery, or fetal mortality with the use of topical corticosteroids of any potency. However, when the dispensed amount of potent or very potent topical corticosteroids exceeded 300 g during the entire pregnancy, maternal use was associated with an increased risk of low birth weight in infants.

Animal Data
Clobetasol propionate is absorbed percutaneously, and when administered subcutaneously it caused malformations in both the rabbit and the mouse.

Clobetasol propionate has greater potential for adverse developmental effects than steroids that are less potent.

The effect of clobetasol propionate on pregnancy outcome and development of offspring was studied in the rat. Clobetasol propionate was administered subcutaneously to female rats twice daily (0, 12.5, 25, and 50 μg/kg/day) from day 7 of presumed gestation through day 25 of lactation or day 24 presumed gestation for those rats that did not deliver a litter. The maternal no-observed-adverse-effect-level (NOAEL) for clobetasol propionate was less than 12.5 μg/kg/day due to reduced body weight gain and feed consumption during the gestation period. The reproductive NOAEL in the dams was 25 μg/kg/day based on prolonged delivery at 50 μg/kg/day. The NOAEL for viability and growth in the offspring was 12.5 μg/kg/day based on incidence of stillbirths, reductions in pup body weights on days 1 and 7 of lactation, increased pup mortality, increases in the incidence of umbilical hernia, and increases in the incidence of pups with cysts on the kidney at higher dose levels during the preweaning period. The weights of the epididymides and testes were significantly reduced at higher dosages. Despite these changes, there were no effects on the mating and fertility of the offspring.

8.2 Lactation

Risk Summary
There is no information regarding the presence of clobetasol propionate in human milk or its effects on the breastfed infant or on milk production. It is not known whether topical administration of clobetasol propionate could result in sufficient systemic absorption to produce detectable quantities in human milk. The developmental and health benefits of breastfeeding should be considered along with the mother’s clinical need for CLOBEX® Spray and any potential adverse effects on the breastfed infant from CLOBEX® Spray or from the underlying maternal condition.
Clinical Considerations
To minimize potential exposure to the breastfed infant via breast milk, use CLOBEX® Spray on the smallest area of skin and for the shortest duration possible while breastfeeding. Advise breastfeeding women not to apply CLOBEX® Spray directly to the nipple and areola to avoid direct infant exposure [see Use in Specific Populations (8.4)].

8.3 Pediatric Use

Use in patients under 18 years of age is not recommended, because safety has not been established and because numerically high rates of HPA axis suppression were seen with other clobetasol propionate topical formulations. Safety and effectiveness in pediatric patients treated with CLOBEX®Spray, 0.05% have not been established [see Warnings and Precautions (5.1)] .

Because of higher ratio of skin surface area to body mass, pediatric patients are at a greater risk than adults of HPA axis suppression and Cushing’s syndrome when they are treated with topical corticosteroids. They are therefore also at greater risk of glucocorticosteroid insufficiency during and/or after withdrawal of treatment.
Adverse effects including striae have been reported with inappropriate use of topical corticosteroids in infants and children.

HPA axis suppression, Cushing’s syndrome, linear growth retardation, delayed weight gain, and intracranial hypertension have been reported in children receiving topical corticosteroids. Manifestations of adrenal suppression in children include low plasma cortisol levels and absence of response to ACTH stimulation. Manifestations of intracranial hypertension include bulging fontanelles, headaches, and bilateral papilledema.

8.4 Geriatric Use

Clinical studies of CLOBEX®Spray, 0.05% did not include sufficient numbers of patients aged 65 and over to adequately determine whether they respond differently than younger patients. In two randomized, vehicle controlled clinical trials, 21 of the 240 patients (9%) were over the age of 65. In general, dose selection for an elderly patient should be made with caution, usually starting at the low end of the dosing range, reflecting the greater frequency of decreased hepatic, renal or cardiac function, and of concomitant disease or other drug therapy.

10 OVERDOSAGE

Topically applied CLOBEX®Spray, 0.05% can be absorbed in sufficient amount to produce systemic effects [see Warnings and Precautions (5.1)] .

11 DESCRIPTION

CLOBEX®(clobetasol propionate) Spray, 0.05% contains clobetasol propionate, a synthetic fluorinated corticosteroid, for topical use. The corticosteroids constitute a class of primarily synthetic steroids used topically as anti-inflammatory and antipruritic agents. Clobetasol propionate is 21-chloro-9-fluoro-11β, 17-dihydroxy-16β-methylpregna-1,4-diene-3,20-dione 17-propionate, with the empirical formula C25H32CIFO5, and a molecular weight of 466.97 (CAS Registry Number 25122-46-7).

The following is the chemical structure:

Clobetasol propionate is a white to almost white crystalline powder that is practically insoluble in water. Each gram of CLOBEX®Spray, 0.05% contains 0.5 mg of clobetasol propionate, in a clear, colorless liquid composed of alcohol, isopropyl myristate, sodium lauryl sulfate, and undecylenic acid.

12 CLINICAL PHARMACOLOGY

12.1 Mechanism of Action

Corticosteroids play a role in cellular signaling, immune function, inflammation, and protein regulation; however, the precise mechanism of action in corticosteroid responsive dermatoses is unknown.

12.2 Pharmacodynamics

Vasoconstrictor Assay

CLOBEX®Spray, 0.05% is in the super-high range of potency as demonstrated in a vasoconstrictor study in healthy subjects when compared with other topical corticosteroids. However, similar blanching scores do not necessarily imply therapeutic equivalence.

Hypothalamic-Pituitary-Adrenal (HPA) Axis Suppression

The effect of CLOBEX®Spray, 0.05% on hypothalamic-pituitary-adrenal (HPA) axis function was investigated in adults in two studies. In the first study, patients with plaque psoriasis covering at least 20% of their body applied CLOBEX®Spray, 0.05% twice daily for up to 4 weeks. 15% (2 out of 13) of patients displayed adrenal suppression after 4 weeks of use based on the Cosyntropin Stimulation Test. The laboratory suppression was transient; all subjects returned to normal after cessation of drug use. In the second study, patients with plaque psoriasis covering at least 20% of their body applied CLOBEX®Spray, 0.05% twice daily for either 2 or 4 weeks. 19% (4 out of 21) of patients treated for 2 weeks and 20% (3 out of 15) of patients treated for 4 weeks displayed adrenal suppression at the end of treatment based on the Cosyntropin Stimulation Test. The laboratory suppression was transient; all subjects returned to normal after cessation of drug use. In these studies, HPA axis suppression was defined as serum cortisol level ≤ 18 μg/dL 30-min post cosyntropin (ACTH1-24) stimulation [ see Warnings and Precautions (5)] .

12.3 Pharmacokinetics

The extent of percutaneous absorption of topical corticosteroids is determined by many factors, including the vehicle, the integrity of the epidermal barrier and occlusion.

Topical corticosteroids can be absorbed from normal intact skin. Inflammation and other disease processes in the skin may increase percutaneous absorption.

There are no human data regarding the distribution of corticosteroids to body organs following topical application. Nevertheless, once absorbed through the skin, topical corticosteroids are handled through metabolic pathways similar to systemically administered corticosteroids. They are metabolized, primarily in the liver, and are then excreted by the kidneys. In addition, some corticosteroids and their metabolites are also excreted in the bile.

13 NONCLINICAL TOXICOLOGY

13.1 Carcinogenesis, Mutagenesis, Impairment of Fertility

Clobetasol propionate was not carcinogenic to rats when topically applied for 2 years at concentrations up to 0.005% which corresponded to doses up to 11 μg/kg/day.

Clobetasol propionate was negative in the in vitro mammalian chromosomal aberration test and in the in vivo mammalian erythrocyte micronucleus test
The effect of subcutaneously administered clobetasol propionate on fertility and general reproductive toxicity was studied in rats at doses of 0, 12.5, 25, and 50 μg/kg/day. Males were treated beginning 70 days before mating and females beginning 15 days before mating through day 7 of gestation. A dosage level of less than 12.5 μg/kg/day clobetasol propionate was considered to be the NOAEL for paternal and maternal general toxicity based on decreased weight gain and for male reproductive toxicity based on increased weights of fluid-filled seminal vesicles. The female reproductive NOAEL was 12.5 μg/kg/day based on reduction in the numbers of estrous cycles during the pre-cohabitation period and an increase in the number of nonviable embryos at higher doses.

14 CLINICAL STUDIES

The efficacy of CLOBEX®Spray, 0.05% in psoriasis has been demonstrated in two randomized, vehicle controlled clinical trials, which were identical in design. The studies were conducted in patients aged 18 years and older with moderate to severe plaque psoriasis. Patients were treated twice daily for up to 4 weeks with either CLOBEX®Spray, 0.05% or vehicle spray.

Patients were evaluated on their Overall Disease Severity, a 5-point scale based on scaling, erythema, and plaque elevation that classified subjects as clear, almost clear, mild, moderate, or severe/very severe. Only patients classified as moderate or severe/very severe at baseline were enrolled in the studies. The median percent body surface area (BSA) at baseline was 6% for the two studies. The numbers of patients scored as clear or almost clear at Weeks 2 and 4 are presented in Table 2.

Table 2: Number of Patients Clear or Almost Clear on Overall Disease Severity Sale at Weeks 2 & 4
 | Study 1 |  | Study 2
 | Clobex® N=60 | Vehicle N=60 | Clobex® N=60 | Vehicle N=60
Week 2 Clear Almost Clear | 1 (2%) 32 (53%) | 0 (0%) 1 (2%) | 0 (0%) 28 (47%) | 0 (0%) 0 (0%)
Week 4 Clear Almost Clear | 15 (25%) 32 (53%) | 0 (0%) 2 (3%) | 18 (30%) 31 (52%) | 0 (0%) 1 (2%)

16 HOW SUPPLIED/STORAGE AND HANDLING

CLOBEX®Spray, 0.05% is a clear, colorless liquid, supplied in a white HDPE bottle with a white polypropylene cap and white LDPE liner in the following sizes:

2 fl oz/59 mL NDC0299-3849-02

4.25 fl oz/125 mL NDC0299-3849-04

Storage:Keep tightly closed. Store under controlled room temperature conditions 20°C to 25°C (68°F to 77°F) with excursions permitted between 15°C and 30°C (59°F and 86°F). Do not freeze, refrigerate or store above 30°C. Spray is flammable; avoid heat, flame or smoking when using this product.

17 PATIENT COUNSELING INFORMATION

[See FDA-approved patient labeling (Patient Information)]

17.1 Information for Patients

Patients using topical corticosteroids should receive the following information and instructions:

- This medication is to be used as directed by the physician and should not be used longer than the prescribed time period.
- This medication should not be used for any disorder other than that for which it was prescribed.
- Do not use other corticosteroid-containing products while using CLOBEX®Spray, 0.05% unless directed by your physician.
- The treated skin area should not be bandaged, otherwise covered, or wrapped so as to be occlusive unless directed by the physician.
- Patients should wash their hands after applying the medication.
- Advise patients to report any visual symptoms to their healthcare providers.
- Patients should report any signs of local or systemic adverse reactions to the physician.
- Patients should inform their physicians that they are using CLOBEX®Spray, 0.05% if surgery is contemplated.
- If you go to another doctor for illness, injury or surgery, tell that doctor you are using CLOBEX®Spray, 0.05%.
- This medication is for external use only. It should not be used on the face, underarms, or groin area. Also avoid contact with the eyes and lips.
- As with other corticosteroids, therapy should be discontinued when control is achieved. If no improvement is seen within 2 weeks, contact the physician.
- Advise a woman to use CLOBEX Spray on the smallest area of skin and for the shortest duration possible while pregnant or breastfeeding. Advise breastfeeding women not to apply CLOBEX Spray directly to the nipple and areola to avoid direct infant exposure
- Patients should not use more than 50 g (59 mL or 2 fl.oz.) per week of CLOBEX®Spray, 0.05%.
- Do not use more than 26 sprays per application or 52 sprays per day.
- This medication is flammable; avoid heat, flame or smoking when applying this product.

17.2 Instructions to the Pharmacist

1. Remove the spray pump from the wrapper
2. Remove and discard the cap from the bottle
3. Keeping the bottle vertical, insert the spray pump into the bottle and turn clockwise until well-fastened
4. Dispense the bottle with the spray pump inserted

PATIENT INFORMATION CLOBEX® (KLO-bex) (clobetasol propionate) Spray

Important: For use on skin only. Do not get CLOBEX® Spray near or in your mouth, eyes or vagina.

Read the Patient Information that comes with CLOBEX® Spray before you start using it and each time you get a refill. There may be new information. This information does not take the place of talking with your doctor about your medical condition or your treatment.

What is CLOBEX® Spray?
CLOBEX® Spray is a prescription corticosteroid medicine used to treat adults with moderate to severe plaque psoriasis that affects up to 20% of the body’s skin surface. CLOBEX® Spray is for use on the skin only (topical).

- CLOBEX® Spray should only be used for the shortest amount of time needed to treat your plaque psoriasis.
- Do not use more than 26 sprays for each application or more than 52 sprays in 1 day.
- You should not apply more than 59 mL (2 fluid ounces) of CLOBEX® Spray to your skin in 1 week.

You should not use CLOBEX® Spray:
• on your face, under arms (armpits), or groin areas
• if you have thinning of the skin (atrophy) at the treatment site
• to treat rosacea or a rash around the mouth (perioral dermatitis)
It is not known if CLOBEX® Spray is safe and effective in children under 18 years of age. CLOBEX® Spray should not be used in children under 18 years of age.

What should I tell my doctor before using CLOBEX® Spray?
Before you use CLOBEX® Spray, tell your doctor if you:
• have a skin infection. You may need medicine to treat the skin infection before you use CLOBEX® Spray.
• plan to have surgery.
• have any other medical conditions.
• are pregnant or plan to become pregnant. It is not known if CLOBEX® Spray will harm your unborn baby.
• are breast-feeding or plan to breast-feed. It is not known if CLOBEX® Spray passes into your breast milk. Talk to your doctor about the best way to feed your baby if you use CLOBEX® Spray.

Tell your doctor about all the medicines you take, including prescription and non-prescription medicines, vitamins, and herbal supplements. Especially tell your doctor if you take other corticosteroid medicines by mouth or use other products on your skin that contain corticosteroids. Ask your doctor or pharmacist if you are not sure.
Know the medicines you take. Keep a list of them to show your doctor and pharmacist when you get a new medicine.

How should I use CLOBEX® Spray?
• Use CLOBEX® Spray exactly as your doctor tells you to use it.
• Your doctor should tell you how much CLOBEX® Spray to use and where to apply it.
• CLOBEX® Spray is for use on skin only. Do not get CLOBEX® Spray near or in your eyes, mouth, or vagina.
• You should not use CLOBEX® Spray on your face, underarms (armpits), or groin areas.
• Apply CLOBEX® Spray 2 times each day.
• Apply only enough CLOBEX® Spray to cover the affected skin areas. Rub in gently and completely.
• Wash your hands after using CLOBEX® Spray.
• Throw away any unused CLOBEX® Spray.
• Do not bandage or cover your treated areas unless your doctor tells you to.
• Tell your doctor if your skin condition is not getting better after 2 weeks of using CLOBEX®Spray. Your doctor may tell you to apply CLOBEX® Spray to certain areas of your skin for up to 2 more weeks if needed. You should not use CLOBEX® Spray for more than 4 weeks unless your doctor tells you to. This can increase your risk of serious side effects.
See the "Instructions for Use" at the end of the Patient Information for detailed information on the right way to apply CLOBEX® Spray.

What should I avoid while using CLOBEX®Spray?
• CLOBEX® Spray is flammable.Avoid heat, flames or smoking while applying CLOBEX® Spray to your skin.

What are the possible side effects of CLOBEX® Spray?
• Clobex® Spray can pass through your skin.Too much Clobex® Spray passing through your skin can cause your adrenal glands to stop working. Your doctor may do blood tests to check how well your adrenal glands are working.
The most common side effects with CLOBEX® Spray include:
• burning at treated site
• upper respiratory tract infection
• runny nose
• sore throat
• dry, itchy, and reddened skin
If you go to another doctor for illness, injury or surgery, tell that doctor you are using Clobex® Spray. Tell your doctor if you have any side effect that bothers you or that does not go away. These are not all the possible side effects of CLOBEX® Spray. For more information, ask your doctor or pharmacist. Call your doctor for medical advice about side effects. You may report side effects to FDA at 1-800-FDA-1088. You may also report side effects to Galderma Laboratories, L.P. at 1-866-735-4137

How should I store CLOBEX® Spray?
• Store CLOBEX® Spray at room temperature between 68°F to 77°F (20°C to 25°C).
• Do not store CLOBEX® Spray above 86°F (30°C).
• Do not freeze or refrigerate CLOBEX® Spray.
• Keep the bottle of CLOBEX® Spray tightly closed.
• Keep away from heat or flame.

Keep CLOBEX® Spray and all medicines out of the reach of children.
General information about CLOBEX® Spray.
Medicines are sometimes prescribed for purposes other than those listed in a Patient Information leaflet. Do not use CLOBEX® Spray for a condition for which it was not prescribed. Do not give CLOBEX® Spray to other people, even if they have the same symptoms that you have. It may harm them.
This Patient Information leaflet summarizes the most important information about CLOBEX® Spray. If you would like more information, talk with your doctor. You can ask your pharmacist or doctor for information about CLOBEX® Spray that is written for health professionals.

What are the ingredients of CLOBEX® Spray?
Activeingredient: clobetasol propionate
Inactiveingredients: alcohol, isopropyl myristate, sodium lauryl sulfate, and undecylenic acid.

Read the Instructions for Use that comes with CLOBEX® Spray before you start using it and each time you get a refill. There may be new information. This information does not take the place of talking with your doctor about your medical condition or your treatment.
Parts of CLOBEX® Spray (See Figure A)
When you receive CLOBEX® Spray the Directional Spray Nozzle is in the “locked” position with the nozzle pointing downwards. (See Figure B)

How to apply CLOBEX® Spray:
Step 1:To unlock the Directional Spray Nozzle, hold the CLOBEX® Spray bottle and sides of the Pump Top with one hand. Use your other hand to turn the Directional Spray Nozzle to either the right or the left. (See Figure C) The spray will come out through the opening at the end of the Directional Spray Nozzle.

Step 2:To apply CLOBEX® Spray, point the Directional Spray Nozzle to the affected area. To spray, push down on the Pump Top. Apply CLOBEX® Spray to the affected area as instructed by your doctor. (See Figure D)

Step 3:Spray only enough CLOBEX® Spray to cover the affected area, for example, the elbow. (See Figure E) Rub in CLOBEX® Spray gently and completely.
• You should not apply CLOBEX® Spray to your face, underarms or groin. Avoid contact with eyes.
• To apply to your scalp, part your hair at the area where CLOBEX® Spray is to be applied. Spray directly on the affected area, and then rub in gently and completely. (See Figure F)
• Repeat Steps 2 and 3 to apply CLOBEX® Spray to other affected areas as instructed by your doctor

Step 4:After applying CLOBEX® Spray, return the Directional Spray Nozzle to the “locked” position. (See Figure G)

Step 5:Wash your hands after applying CLOBEX® Spray.
This Patient Information and Instructions for Use have been approved by the U.S. Food and Drug Administration.
Marketed by:
GALDERMA LABORATORIES, L.P., Dallas, TX 75201 USA
Made in Canada
Revised: 02/2023
All trademarks are the property of their respective owners.
P51011-3

PRINCIPAL DISPLAY PANEL - 4.25 oz CARTON

Rx Only
NDC0299-3849-04
Clobex® (clobetasol propionate) Spray0.05%
For topical use only
4.25 FL OZ
(125 mL)
GALDERMA

WARNING: FLAMMABLE AVOID FIRE, FLAME OR SMOKING DURING AND IMMEDIATELY FOLLOWING APPLICATION
Not for eye use.
Usual dosage:Apply twice daily, once in the morning and once at night.
Use only enough to cover the affected areas. Do not exceed 26 sprays per application or 52 sprays per day. Do not apply to face, underarms, or groin and avoid contact with eyes and lips. See package insert for complete prescribing information. See lot number and expiration date on the bottom of the carton.

TO THE PHARMACIST
● Ensure the patient receives the Patient Information.
● Replace cap with spray pump prior to dispensing.
Each gram contains: Active : clobetasol propionate (0.5 mg).
Inactive:alcohol, isopropyl myristate, sodium lauryl sulfate, and undecylenic acid.
Store at controlled room temperature 68° to 77°F (20° - 25°C), excursions permitted between 59° to 86°F (15° - 30°C).
Protect from freezing.
Do not refrigerate or store above 86° (30°C).
Keep out of reach of children.

Marketed by:
GALDERMA LABORATORIES, L.P.
Dallas, TX 75201 USA
All trademarks are the property of their respective owners.
Made in Canada.
www.clobex.com
P51015-4